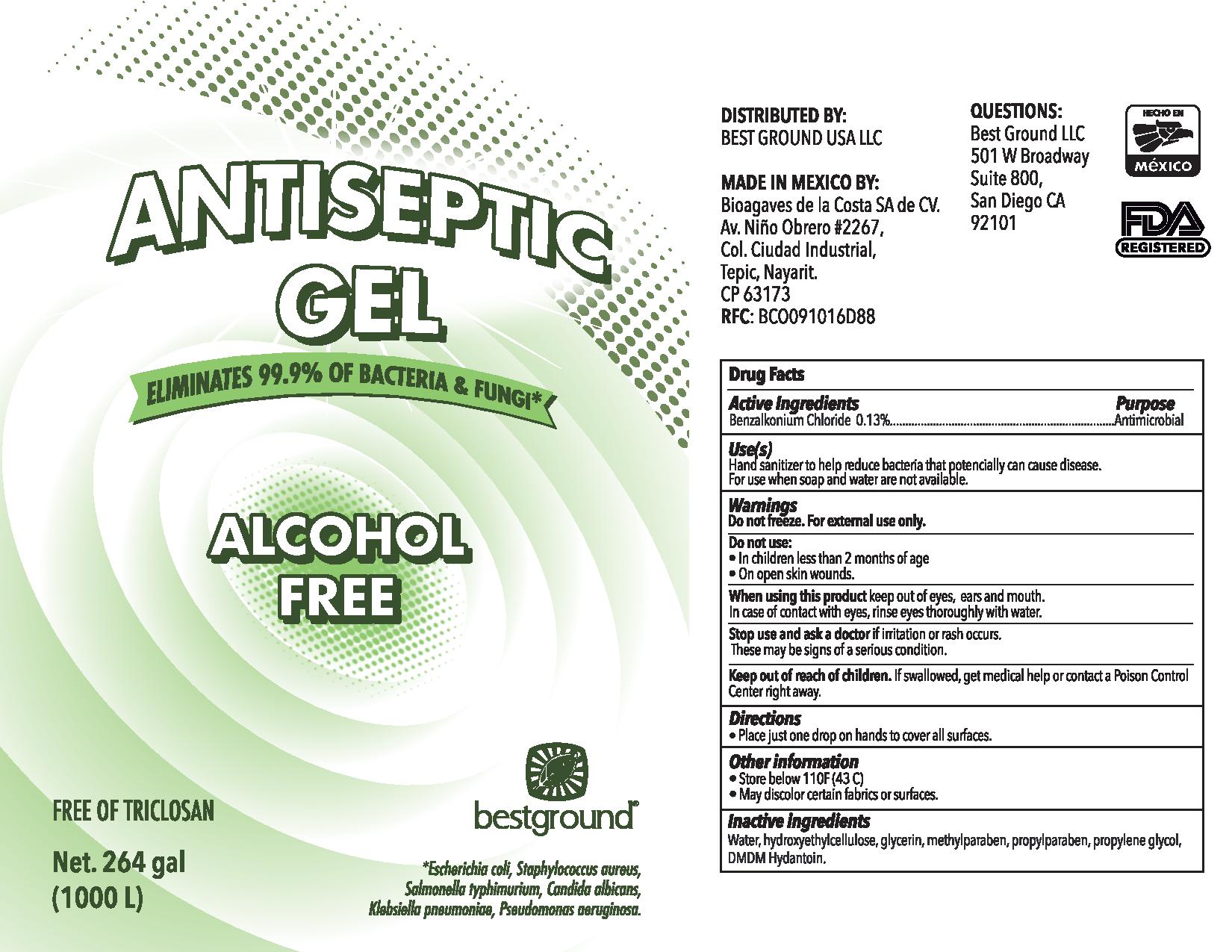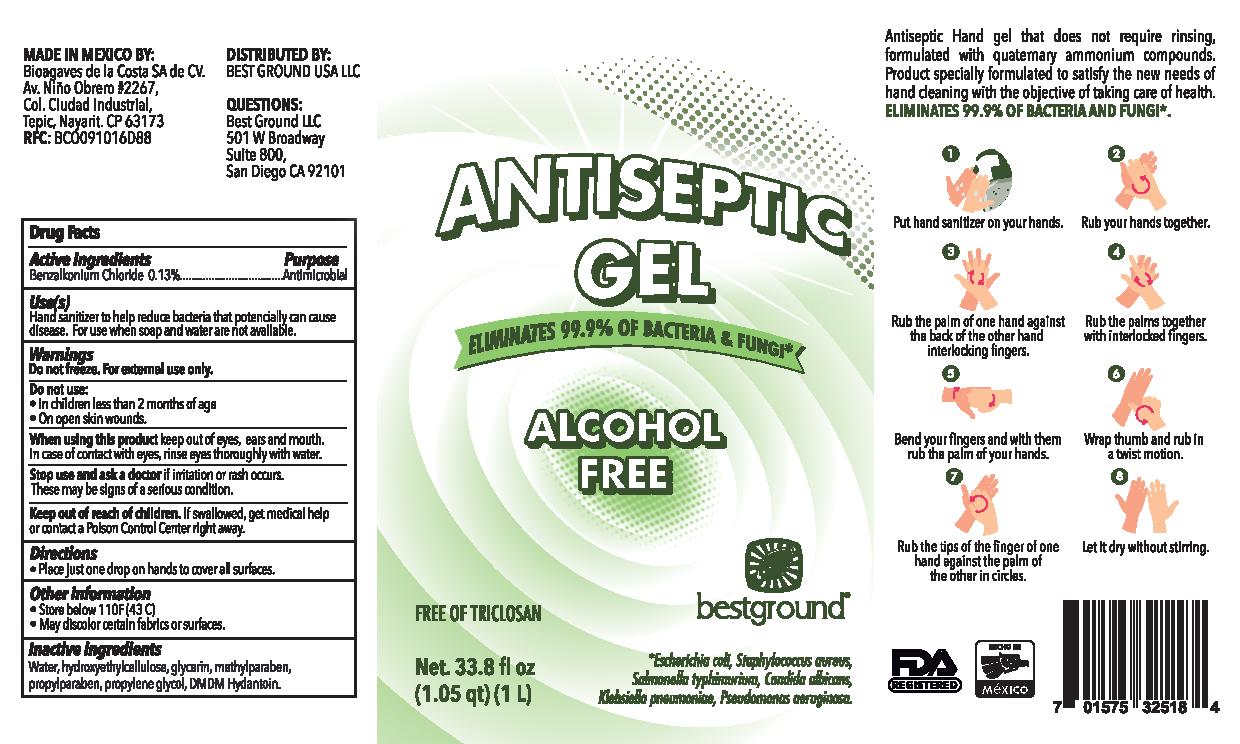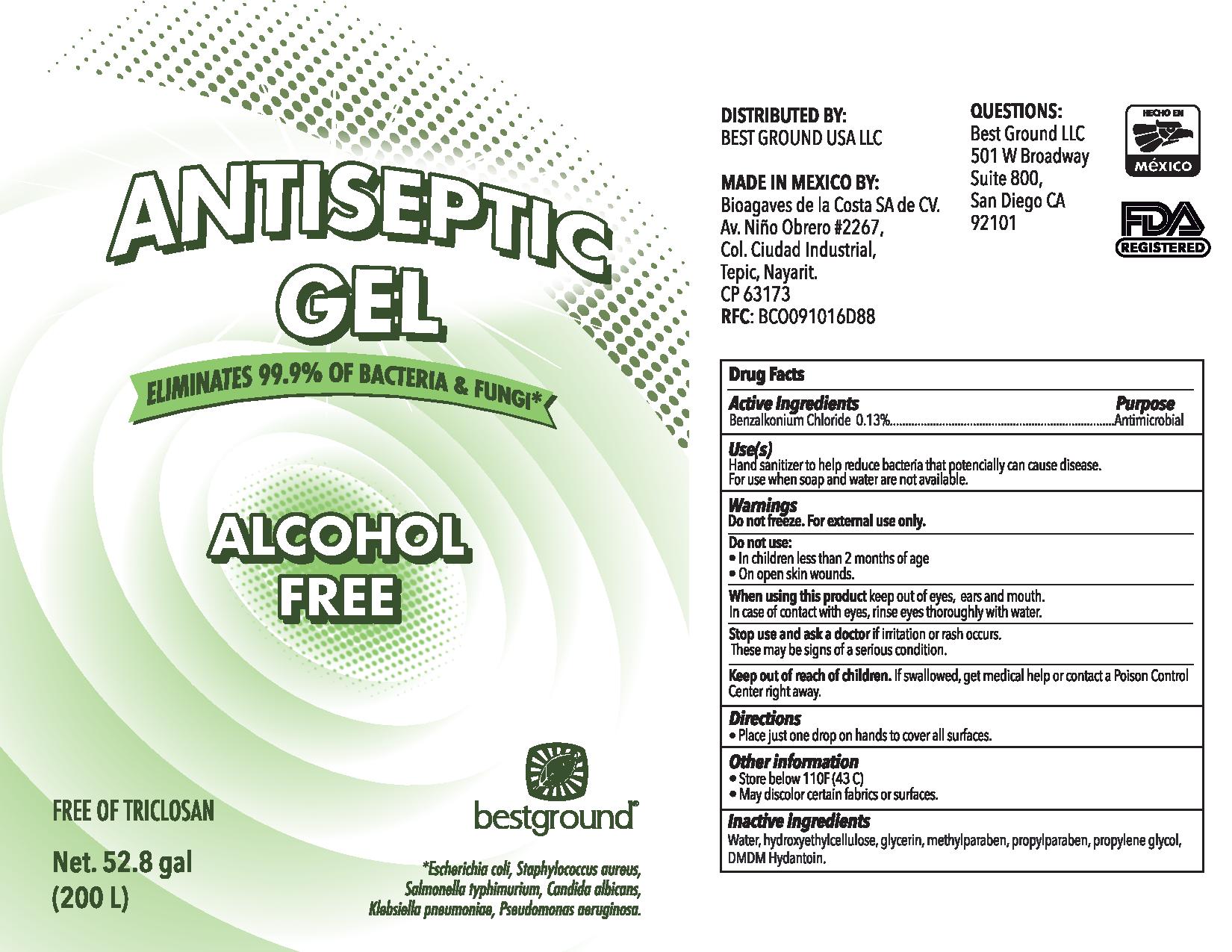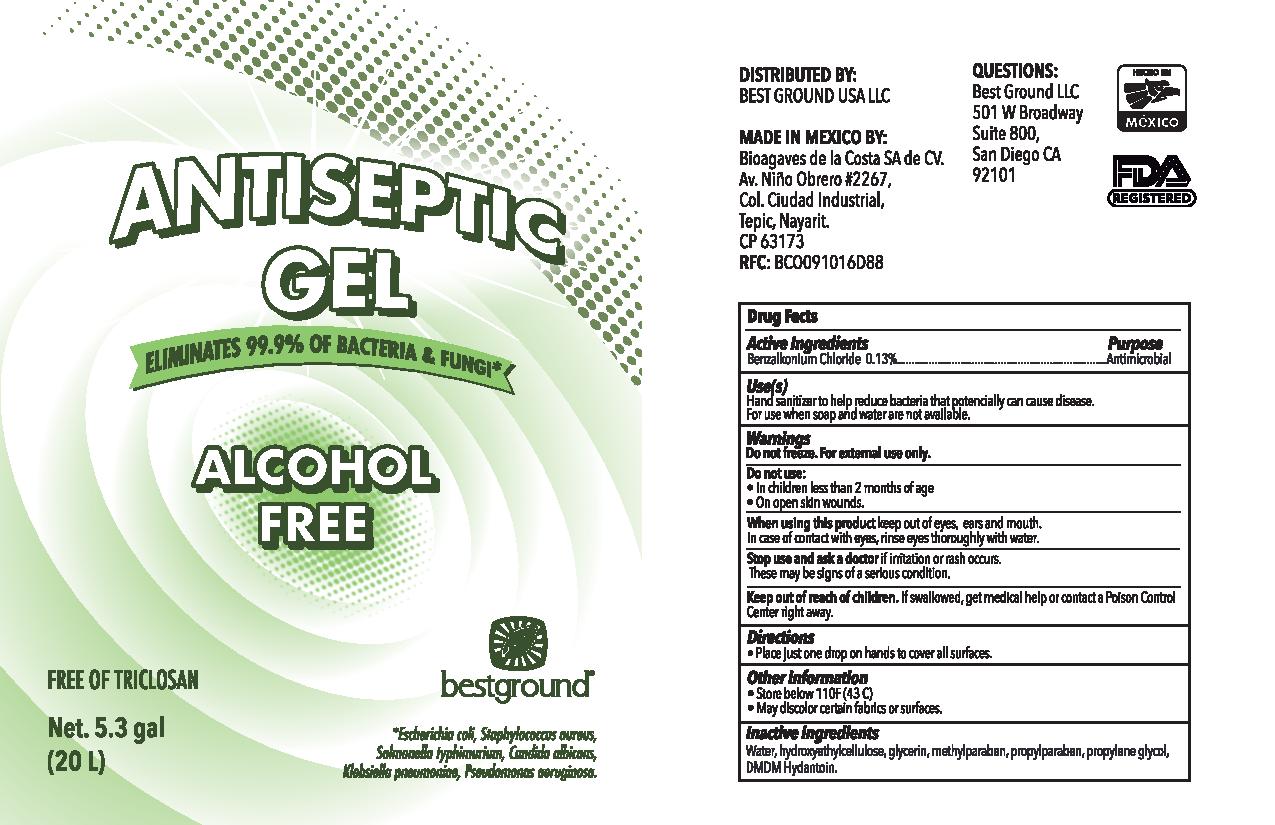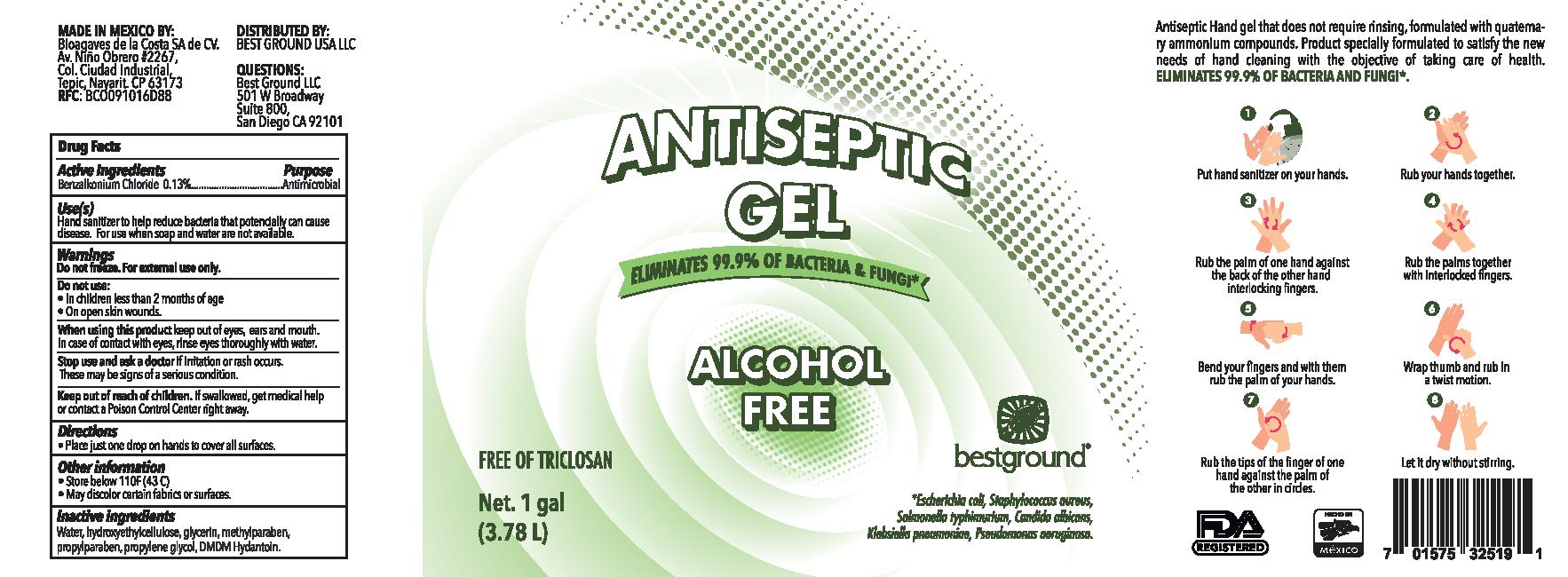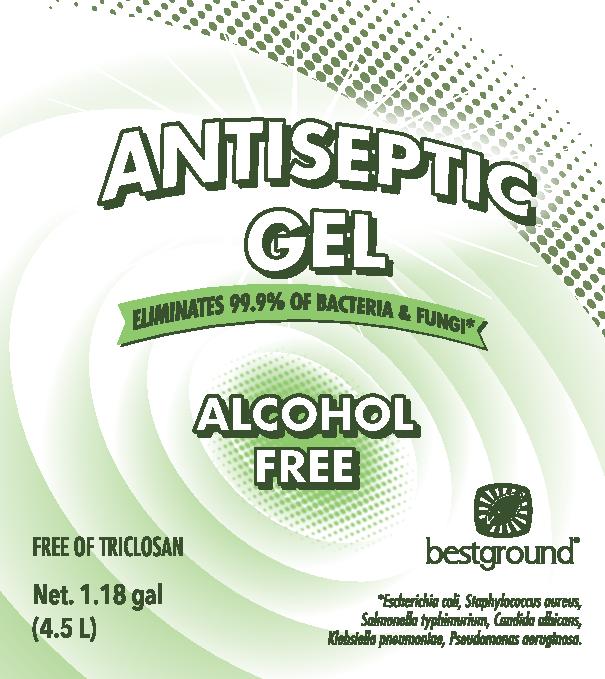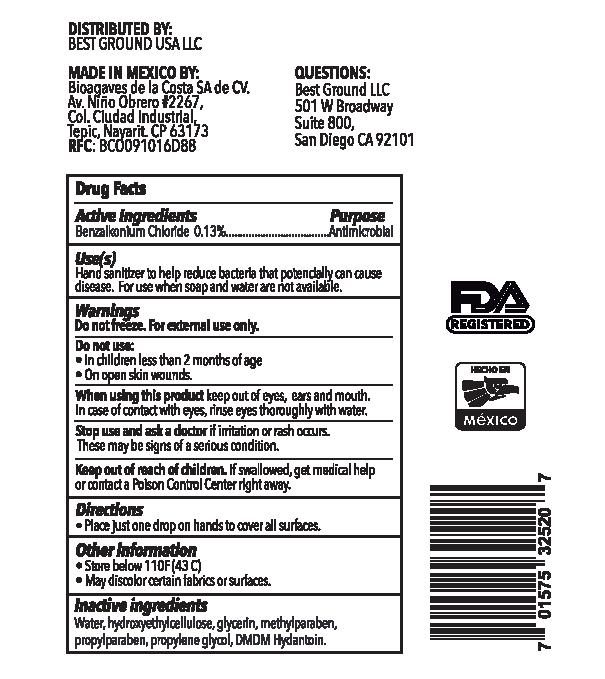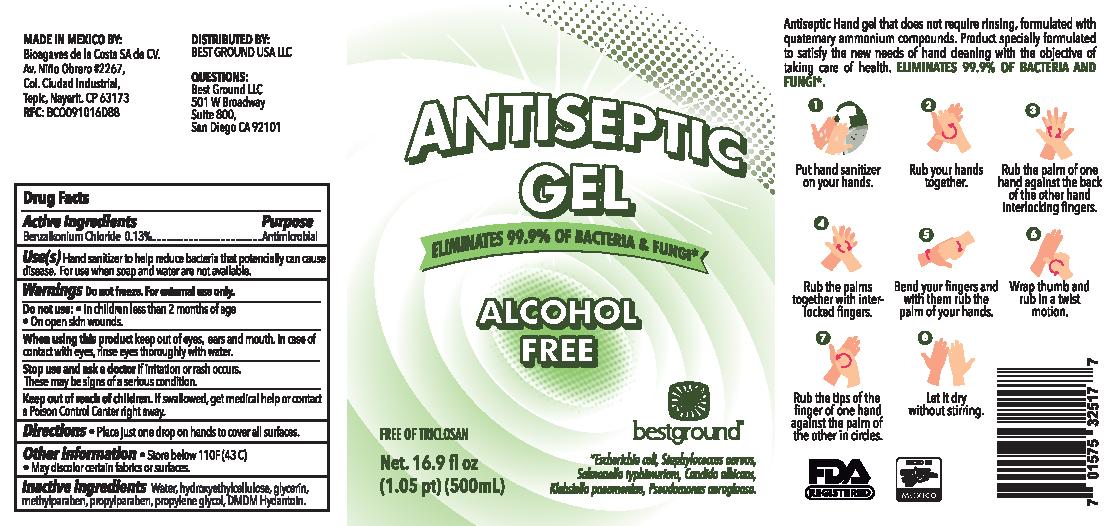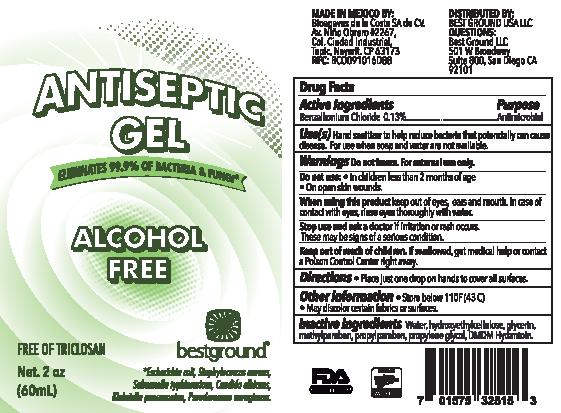 DRUG LABEL: Alcohol-Free Antiseptic Gel
NDC: 76598-010 | Form: GEL
Manufacturer: Bioagaves de la Costa, S.A. de C.V.
Category: otc | Type: HUMAN OTC DRUG LABEL
Date: 20200825

ACTIVE INGREDIENTS: BENZALKONIUM CHLORIDE 13 mg/100 mL
INACTIVE INGREDIENTS: HYDROXYETHYL CELLULOSE, UNSPECIFIED; GLYCERIN; WATER; METHYLPARABEN; PROPYLPARABEN; DMDM HYDANTOIN; PROPYLENE GLYCOL

Active Ingredients

Benzalkonium Chloride 0.13%

Purpose

Antimicrobial

Use

Hand sanitizer to help reduce bacteria that can potencially cause disease.

For use when soap and water are not available.

WARNINGS

Do not freeze. For external use only.

DO NOT USE

- In children less than 2 months of age
- On open skin wounds.

When using this product keep out of eyes, ears and mouth. In case of contact with eyes, rinse eyes thoroughly with water.

Stop use and ask a doctor if irritation or rash occurs.

These may be signs of a serious condition.

Keep out of reach of children.

If swallowed, get medical help or contact a Poison Control Center right away.

Directions

- Place just one drop on hands to cover all surfaces.

OTHER INFORMATION

- Store below 110F (43C)
- May discolor certain fabrics or surfaces

INACTIVE INGREDIENTS

Water, hyroxyethyl cellulose, glycerin, methylparaben, propylene glycol, DMDM H